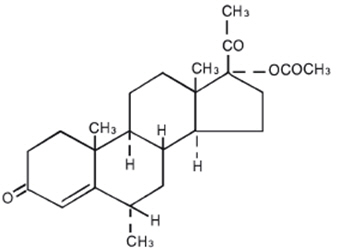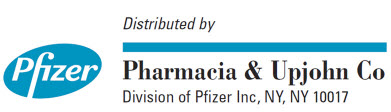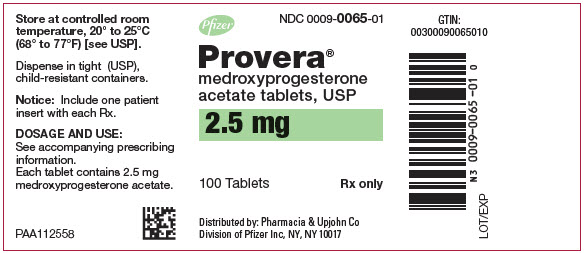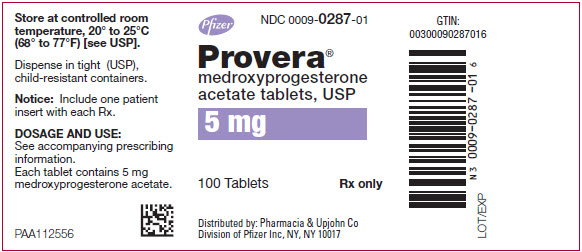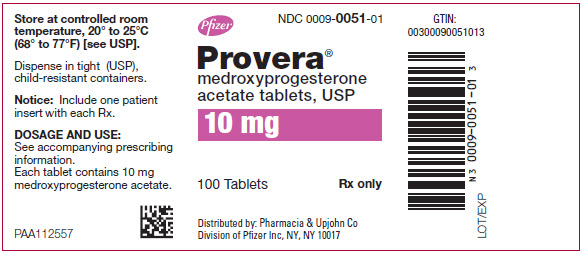 DRUG LABEL: Provera
NDC: 0009-0065 | Form: TABLET
Manufacturer: Pharmacia & Upjohn Company LLC
Category: prescription | Type: HUMAN PRESCRIPTION DRUG LABEL
Date: 20240830

ACTIVE INGREDIENTS: MEDROXYPROGESTERONE ACETATE 2.5 mg/1 1
INACTIVE INGREDIENTS: CALCIUM STEARATE; STARCH, CORN; LACTOSE, UNSPECIFIED FORM; MINERAL OIL; SORBIC ACID; SUCROSE; TALC; FD&C YELLOW NO. 6

PROVERA®
(medroxyprogesterone acetate tablets, USP)

WARNING: CARDIOVASCULAR DISORDERS, BREAST CANCER AND PROBABLE DEMENTIA FOR ESTROGEN PLUS PROGESTIN THERAPY

Cardiovascular Disorders and Probable Dementia

Estrogen plus progestin therapy should not be used for the prevention of cardiovascular disease or dementia. (See CLINICAL STUDIES and WARNINGS, Cardiovascular Disorders and Probable Dementia.)

The Women's Health Initiative (WHI) estrogen plus progestin substudy reported an increased risk of deep vein thrombosis (DVT), pulmonary embolism (PE), stroke and myocardial infarction (MI) in postmenopausal women (50 to 79 years of age) during 5.6 years of treatment with daily oral conjugated estrogens (CE) [0.625 mg] combined with medroxyprogesterone acetate (MPA) [2.5 mg], relative to placebo. (See CLINICAL STUDIES and WARNINGS, Cardiovascular Disorders.)

The WHI Memory Study (WHIMS) estrogen plus progestin ancillary study reported an increased risk of developing probable dementia in postmenopausal women 65 years of age or older during 4 years of treatment with daily CE (0.625 mg) combined with MPA (2.5 mg), relative to placebo. It is unknown whether this finding applies to younger postmenopausal women. (See CLINICAL STUDIES and WARNINGS, Probable Dementia and PRECAUTIONS, Geriatric Use.)

Breast Cancer

The WHI estrogen plus progestin substudy demonstrated an increased risk of invasive breast cancer. (See CLINICAL STUDIES and WARNINGS, Malignant Neoplasm, Breast Cancer.)

In the absence of comparable data, these risks should be assumed to be similar for other doses of CE and MPA, and other combinations and dosage forms of estrogens and progestins.

Progestins with estrogens should be prescribed at the lowest effective doses and for the shortest duration consistent with treatment goals and risks for the individual woman.

DESCRIPTION

PROVERA® tablets contain medroxyprogesterone acetate, which is a derivative of progesterone. It is a white to off-white, odorless crystalline powder, stable in air, melting between 200 and 210°C. It is freely soluble in chloroform, soluble in acetone and in dioxane, sparingly soluble in alcohol and in methanol, slightly soluble in ether, and insoluble in water.

The chemical name for medroxyprogesterone acetate is pregn-4-ene-3, 20-dione, 17-(acetyloxy)-6-methyl-, (6α)-. The structural formula is:

Each PROVERA tablet for oral administration contains 2.5 mg, 5 mg or 10 mg of medroxyprogesterone acetate and the following inactive ingredients:

Calcium stearate, corn starch, lactose, mineral oil, sucrose and talc.

The 2.5 mg tablets also contain: FD&C Yellow No. 6.

The 5 mg tablets also contain: FD&C Blue No.2 – Aluminum Lake.

CLINICAL PHARMACOLOGY

Medroxyprogesterone acetate (MPA) administered orally or parenterally in the recommended doses to women with adequate endogenous estrogen, transforms proliferative into secretory endometrium. Androgenic and anabolic effects have been noted, but the drug is apparently devoid of significant estrogenic activity. While parenterally administered MPA inhibits gonadotropin production, which in turn prevents follicular maturation and ovulation, available data indicate that this does not occur when the usually recommended oral dosage is given as single daily doses.

Pharmacokinetics

The pharmacokinetics of MPA were determined in 20 postmenopausal women following a single-dose administration of eight PROVERA 2.5 mg tablets or a single administration of two PROVERA 10 mg tablets under fasting conditions. In another study, the steady-state pharmacokinetics of MPA were determined under fasting conditions in 30 postmenopausal women following daily administration of one PROVERA 10 mg tablet for 7 days. In both studies, MPA was quantified in serum using a validated gas chromatography-mass spectrometry (GC-MS) method. Estimates of the pharmacokinetic parameters of MPA after single and multiple doses of PROVERA tablets were highly variable and are summarized in Table 1.

Table 1. Mean (SD) Pharmacokinetic Parameters for Medroxyprogesterone Acetate (MPA)
Tablet Strength | C max (ng/mL) | T max (h) | Auc 0–(∞) (ng∙h/mL) | t 1/2 (h) | Vd/f (L) | CL/f (mL/min)
Single Dose
2 × 10 mg | 1.01 (0.599) | 2.65 (1.41) | 6.95 (3.39) | 12.1 (3.49) | 78024 (47220) | 64110 (42662)
8 × 2.5 mg | 0.805 (0.413) | 2.22 (1.39) | 5.62 (2.79) | 11.6 (2.81) | 62748 (40146) | 74123 (35126)
Multiple Dose
10 mg [Following Day 7 dose] | 0.71 (0.35) | 2.83 (1.83) | 6.01 (3.16) | 16.6 (15.0) | 40564 (38256) | 41963 (38402)

A. Absorption:

No specific investigation on the absolute bioavailability of MPA in humans has been conducted. MPA is rapidly absorbed from the gastrointestinal tract, and maximum MPA concentrations are obtained between 2 to 4 hours after oral administration.

Administration of PROVERA with food increases the bioavailability of MPA. A 10 mg dose of PROVERA, taken immediately before or after a meal, increased MPA Cmax (50 to 70%) and AUC (18 to 33%). The half-life of MPA was not changed with food.

B. Distribution:

MPA is approximately 90% protein bound, primarily to albumin; no MPA binding occurs with sex hormone binding globulin.

C. Metabolism:

Following oral dosing, MPA is extensively metabolized in the liver via hydroxylation, with subsequent conjugation and elimination in the urine.

D. Excretion:

Most MPA metabolites are excreted in the urine as glucuronide conjugates with only minor amounts excreted as sulfates.

E. Specific Populations

Hepatic Insufficiency

MPA is almost exclusively eliminated via hepatic metabolism. In 14 patients with advanced liver disease, MPA disposition was significantly altered (reduced elimination). In patients with fatty liver, the mean percent dose excreted in the 24-hour urine as intact MPA after a 10 mg or 100 mg dose was 7.3% and 6.4%, respectively.

Renal Insufficiency

The effect of renal impairment on the pharmacokinetics of PROVERA has not been studied.

F. Drug Interactions

Medroxyprogesterone acetate (MPA) is metabolized in-vitro primarily by hydroxylation via the CYP3A4. Specific drug-drug interaction studies evaluating the clinical effects with CYP3A4 inducers or inhibitors on MPA have not been conducted. Inducers and/or inhibitors of CYP3A4 may affect the metabolism of MPA.

CLINICAL STUDIES

Effects on the Endometrium

In a 3-year, double-blind, placebo-controlled study of 356 nonhysterectomized, postmenopausal women between 45 and 64 years of age randomized to receive placebo (n=119), 0.625 mg conjugated estrogen only (n=119), or 0.625 mg conjugated estrogen plus cyclic PROVERA (n=118), results showed a reduced risk of endometrial hyperplasia in the treatment group receiving 10 mg PROVERA plus 0.625 mg conjugated estrogens compared to the group receiving 0.625 mg conjugated estrogens only. See Table 2.

Table 2. Number (%) of Endometrial Biopsy Changes Since Baseline After 3 Years of Treatment [Includes most extreme abnormal result]
Histological Results | Placebo (n=119) | CEE [CEE = conjugated equine estrogens 0.625 mg/day] (n=119) | PROVERA [PROVERA = medroxyprogesterone acetate tablets 10 mg/day for 12 days] + CEE (n=118)
Normal/No hyperplasia (%) | 116 (97) | 45 (38) | 112 (95)
Simple (cystic) hyperplasia (%) | 1 (1) | 33 (28) | 4 (3)
Complex (adenomatous) hyperplasia (%) | 1 (1) | 27 (22) | 2 (2)
Atypia (%) | 0 | 14 (12) | 0
Adenocarcinoma (%) | 1 (1) | 0 | 0

In a second 1-year study, 832 postmenopausal women between 45 and 65 years of age were treated with daily 0.625 mg conjugated estrogen (days 1–28), plus either 5 mg cyclic PROVERA or 10 mg cyclic PROVERA (days 15–28), or daily 0.625 mg conjugated estrogen only. The treatment groups receiving 5 or 10 mg cyclic PROVERA (days 15–28) plus daily conjugated estrogens showed a significantly lower rate of hyperplasia as compared to the conjugated estrogens only group. See Table 3.

Table 3. Number (%) of Women with Endometrial Hyperplasia at 1 Year
 | CEE [CEE = conjugated equine estrogen 0.625 mg every day of a 28-day cycle.] | MPA [Cyclic medroxyprogesterone acetate on days 15 to 28] + CEE
 | (n=283) | MPA 5 mg (n=277) | MPA 10 mg (n=272)
Cystic hyperplasia (%) | 55 (19) | 3 (1) | 0
Adenomatous hyperplasia without atypia | 2 (1) | 0 | 0

Women's Health Initiative Studies

The WHI enrolled approximately 27,000 predominantly healthy postmenopausal women in two substudies to assess the risks and benefits of daily oral CE (0.625 mg)-alone or in combination with MPA (2.5 mg) compared to placebo in the prevention of certain chronic diseases. The primary endpoint was the incidence of coronary heart disease (CHD) (defined as nonfatal MI, silent MI and CHD death), with invasive breast cancer as the primary adverse outcome. A "global index" included the earliest occurrence of CHD, invasive breast cancer, stroke, PE, endometrial cancer (only in the CE plus MPA substudy), colorectal cancer, hip fracture, or death due to other cause. These substudies did not evaluate the effects of CE-alone or CE plus MPA on menopausal symptoms.

WHI Estrogen Plus Progestin Substudy

The WHI estrogen plus progestin substudy was stopped early. According to the predefined stopping rule, after an average follow-up of 5.6 years of treatment, the increased risk of invasive breast cancer and cardiovascular events exceeded the specified benefits included in the "global index." The absolute excess risk of events included in the "global index" was 19 per 10,000 women-years.

For those outcomes included in the WHI "global index" that reached statistical significance after 5.6 years of follow-up, the absolute excess risks per 10,000 women-years in the group treated with CE plus MPA were 7 more CHD events, 8 more strokes, 10 more PEs, and 8 more invasive breast cancers, while the absolute risk reduction per 10,000 women-years were 6 fewer colorectal cancers and 5 fewer hip fractures.

Results of the CE plus MPA substudy, which included 16,608 women (average 63 years of age, range 50 to 79; 83.9 percent White, 6.8 percent Black, 5.4 percent Hispanic, 3.9 percent Other) are presented in Table 4. These results reflect centrally adjudicated data after an average follow-up of 5.6 years.

Table 4 : RELATIVE AND ABSOLUTE RISK SEEN IN THE ESTROGEN PLUS PROGESTIN SUBSTUDY OF WHI AT AN AVERAGE OF 5.6 YEARS [Adapted from numerous WHI publications. WHI publications can be viewed at www.nhlbi.nih.gov/whi.] , [Results are based on centrally adjudicated data.]
Event | Relative Risk CE/MPA vs placebo (95%nCI [Nominal confidence intervals unadjusted for multiple looks and multiple comparisons.]) | CE/MPA n = 8,506 | Placebo n = 8,102
Event | Relative Risk CE/MPA vs placebo (95%nCI [Nominal confidence intervals unadjusted for multiple looks and multiple comparisons.]) | Absolute Risk per 10,000 Women-Years
CHD events | 1.23 (0.99–1.53) | 41 | 34
Non-fatal MI | 1.28 (1.00–1.63) | 31 | 25
CHD death | 1.10 (0.70–1.75) | 8 | 8
All strokes | 1.31 (1.03–1.68) | 33 | 25
Ischemic stroke | 1.44 (1.09–1.90) | 26 | 18
Deep vein thrombosis [Not included in "global index".] | 1.95 (1.43–2.67) | 26 | 13
Pulmonary embolism | 2.13 (1.45–3.11) | 18 | 8
Invasive breast cancer [Includes metastatic and non-metastatic breast cancer, with the exception of in situ breast cancer.] | 1.24 (1.01–1.54) | 41 | 33
Colorectal cancer | 0.61 (0.42–0.87) | 10 | 16
Endometrial cancer | 0.81 (0.48–1.36) | 6 | 7
Cervical cancer | 1.44 (0.47–4.42) | 2 | 1
Hip fracture | 0.67 (0.47–0.96) | 11 | 16
Vertebral fractures | 0.65 (0.46–0.92) | 11 | 17
Lower arm/wrist fractures | 0.71 (0.59–0.85) | 44 | 62
Total fractures | 0.76 (0.69–0.83) | 152 | 199
Overall mortality [All deaths, except from breast or colorectal cancer, definite or probable CHD, PE or cerebrovascular disease.] | 1.00 (0.83–1.19) | 52 | 52
Global Index [A subset of the events was combined in a "global index", defined as the earliest occurrence of CHD events, invasive breast cancer, stroke, pulmonary embolism, colorectal cancer, hip fracture, or death due to other causes.] | 1.13 (1.02–1.25) | 184 | 165

Timing of the initiation of estrogen plus progestin therapy relative to the start of menopause may affect the overall risk benefit profile. The WHI estrogen plus progestin substudy stratified by age showed in women 50 to 59 years of age a nonsignificant trend toward reduced risk in overall mortality [hazard ration (HR) 0.69 (95 percent CI, 0.44–1.07)].

Women's Health Initiative Memory Study

The WHIMS estrogen plus progestin ancillary study of WHI enrolled 4,532 predominantly healthy postmenopausal women 65 years of age and older (47 percent were aged 65 to 69 years of age, 35 percent were 70 to 74 years of age, and 18 percent were 75 years of age and older) to evaluate the effects of daily CE (0.625 mg) plus MPA (2.5 mg) on the incidence of probable dementia (primary outcome) compared to placebo.

After an average follow-up of 4 years, the relative risk of probable dementia for CE plus MPA versus placebo was 2.05 (95 percent CI, 1.21–3.48). The absolute risk of probable dementia for CE plus MPA versus placebo was 45 versus 33 per 10,000 women-years. Probable dementia as defined in this study included Alzheimer's disease (AD), vascular dementia (VaD) and mixed type (having features of both AD and VaD). The most common classification of probable dementia in the treatment group and the placebo group was AD. Since the ancillary study was conducted in women 65 to 79 years of age, it is unknown whether these findings apply to younger postmenopausal women. (See WARNINGS, Probable Dementia and PRECAUTIONS, Geriatric Use).

INDICATIONS AND USAGE

PROVERA tablets are indicated for the treatment of secondary amenorrhea and abnormal uterine bleeding due to hormonal imbalance in the absence of organic pathology, such as fibroids or uterine cancer. They are also indicated for use in the prevention of endometrial hyperplasia in nonhysterectomized postmenopausal women who are receiving daily oral conjugated estrogens 0.625 mg tablets.

CONTRAINDICATIONS

PROVERA is contraindicated in women with any of the following conditions:

1. Undiagnosed abnormal genital bleeding.
2. Known, suspected, or history of breast cancer.
3. Known or suspected estrogen- or progesterone-dependent neoplasia.
4. Active DVT, PE, or a history of these conditions
5. Active arterial thromboembolic disease (for example, stroke and MI), or a history of these conditions.
6. Known anaphylactic reaction or angioedema to PROVERA.
7. Known liver impairment or disease.
8. Known or suspected pregnancy.

WARNINGS

See BOXED WARNINGS.

1. Cardiovascular Disorders

An increased risk of PE, DVT, stroke, and MI has been reported with estrogen plus progestin therapy. Should any of these events occur or be suspected, estrogen plus progestin therapy should be discontinued immediately.

Risk factors for arterial vascular disease (for example, hypertension, diabetes mellitus, tobacco use, hypercholesterolemia, and obesity) and/or venous thromboembolism (VTE) (for example, personal history or family history of VTE, obesity, and systemic lupus erythematosus) should be managed appropriately.

a. Stroke

In the WHI estrogen plus progestin substudy, a statistically significant increased risk of stroke was reported in women 50 to 79 years of age receiving CE (0.625 mg) plus MPA (2.5 mg) compared to women in the same age group receiving placebo (33 versus 25 per 10,000 women-years). (See CLINICAL STUDIES.) The increase in risk was demonstrated after the first year and persisted. Should a stroke occur or be suspected, estrogen plus progestin therapy should be discontinued immediately.

b. Coronary Heart Disease

In the WHI estrogen plus progestin substudy, there was a statistically non-significant increased risk of CHD events reported in women receiving daily CE (0.625 mg) plus MPA (2.5 mg) compared to women receiving placebo (41 versus 34 per 10,000 women-years). An increase in relative risk was demonstrated in year 1, and a trend toward decreasing relative risk was reported in years 2 through 5.

In postmenopausal women with documented heart disease (n = 2,763, average 66.7 years of age), in a controlled clinical trial of secondary prevention of cardiovascular disease (Heart and Estrogen/Progestin Replacement Study [HERS]), treatment with daily CE (0.625 mg) plus MPA (2.5mg) demonstrated no cardiovascular benefit. During an average follow-up of 4.1 years, treatment with CE plus MPA did not reduce the overall rate of CHD events in postmenopausal women with established coronary heart disease. There were more CHD events in the CE plus MPA-treated group than in the placebo group in year 1, but not during the subsequent years. Two thousand three hundred and twenty-one (2,321) women from the original HERS trial agreed to participate in an open label extension of HERS, HERS II. Average follow-up in HERS II was an additional 2.7 years, for a total of 6.8 years overall. Rates of CHD events were comparable among women in the CE plus MPA group and the placebo group in HERS, HERS II, and overall.

c. Venous Thromboembolism

In the WHI estrogen plus progestin substudy, a statistically significant 2-fold greater rate of VTE (DVT and PE) was reported in women receiving daily CE (0.625 mg) plus MPA (2.5 mg) compared to women receiving placebo (35 versus 17 per 10,000 women-years). Statistically significant increases in risk for both DVT (26 versus 13 per 10,000 women-years) and PE (18 versus 8 per 10,000 women-years) were also demonstrated. The increase in VTE risk was demonstrated during the first year and persisted. (See CLINICAL STUDIES.) Should a VTE occur or be suspected, estrogen plus progestin therapy should be discontinued immediately.

If feasible, estrogens plus progestins should be discontinued at least 4 to 6 weeks before surgery of the type associated with an increased risk of thromboembolism, or during periods of prolonged immobilization.

2. Malignant Neoplasms

a. Breast Cancer

The WHI substudy of daily CE (0.625 mg)-alone provided information about breast cancer in estrogen-alone users. In the WHI estrogen-alone substudy, after an average follow-up of 7.1 years, daily CE-alone was not associated with an increased risk of invasive breast cancer [relative risk (RR) 0.80] compared to placebo (see CLINICAL STUDIES).

After a mean follow-up of 5.6 years, the estrogen plus progestin substudy reported an increased risk of invasive breast cancer in women who took daily CE plus MPA. In this substudy, prior use of estrogen-alone or estrogen plus progestin therapy was reported by 26 percent of the women. The relative risk of invasive breast cancer was 1.24, and the absolute risk was 41 versus 33 cases per 10,000 women-years, for CE plus MPA compared with placebo. Among women who reported prior use of hormone therapy, the relative risk of invasive breast cancer was 1.86, and the absolute risk was 46 versus 25 cases per 10,000 women-years, for CE plus MPA compared with placebo. Among women who reported no prior use of hormone therapy, the relative risk of invasive breast cancer was 1.09, and the absolute risk was 40 versus 36 cases per 10,000 women-years, for CE plus MPA compared with placebo. In the same substudy, invasive breast cancers were larger, were more likely to be node positive, and were diagnosed at a more advanced stage in the CE (0.625 mg) plus MPA (2.5 mg) group compared with the placebo group. Metastatic disease was rare with no apparent difference between the two groups. Other prognostic factors such as histologic subtype, grade, and hormone receptor status did not differ between the groups. (See CLINICAL STUDIES.)

Consistent with the WHI clinical trials, observational studies have also reported an increased risk of breast cancer for estrogen plus progestin therapy, and a smaller, increased risk for estrogen-alone therapy, after several years of use. One large meta-analysis of prospective cohort studies reported increased risks that were dependent upon duration of use and could last up to >10 years after discontinuation of estrogen plus progestin therapy and estrogen-alone therapy. Extension of the WHI trials also demonstrated increased breast cancer risk associated with estrogen plus progestin therapy. Observational studies also suggest that the risk of breast cancer was greater, and became apparent earlier, with estrogen plus progestin therapy as compared to estrogen-alone therapy. However, these studies have not found significant variation in the risk of breast cancer among different estrogen plus progestin combinations, or routes of administration.

The use of estrogen-alone and estrogen plus progestin has been reported to result in an increase in abnormal mammograms requiring further evaluation.

All women should receive yearly breast examinations by a healthcare provider and perform monthly breast self-examinations. In addition, mammography examinations should be scheduled based on patient age, risk factors, and prior mammogram results.

b. Endometrial Cancer

An increased risk of endometrial cancer has been reported with the use of unopposed estrogen therapy in women with a uterus. The reported endometrial cancer risk among unopposed estrogen users is about 2 to 12 times greater than in non-users, and appears dependent on duration of treatment and on estrogen dose. Most studies show no significant increased risk associated with the use of estrogens for less than 1 year. The greatest risk appears associated with prolonged use, with increased risks of 15- to 24-fold for 5 to 10 years or more. This risk has been shown to persist for at least 8 to 15 years after estrogen therapy is discontinued.

Clinical surveillance of all women using estrogen plus progestin therapy is important. Adequate diagnostic measures, including endometrial sampling when indicated, should be undertaken to rule out malignancy in all cases of undiagnosed persistent or recurring abnormal genital bleeding. There is no evidence that the use of natural estrogens results in a different endometrial risk profile than synthetic estrogens of equivalent estrogen dose. Adding a progestin to estrogen therapy has been shown to reduce the risk of endometrial hyperplasia, which may be a precursor to endometrial cancer.

c. Ovarian Cancer

The WHI estrogen plus progestin substudy reported a statistically non-significant increased risk of ovarian cancer. After an average follow-up of 5.6 years, the relative risk for ovarian cancer for CE plus MPA versus placebo was 1.58 (95 percent CI, 0.77–3.24). The absolute risk for CE plus MPA was 4 versus 3 cases per 10,000 women-years. In some epidemiologic studies, the use of estrogen plus progestin and estrogen-only products, in particular for 5 or more years, has been associated with increased risk of ovarian cancer. However, the duration of exposure associated with increased risk is not consistent across all epidemiologic studies and some report no association.

3. Probable Dementia

In the WHIMS estrogen plus progestin ancillary study of WHI, a population of 4,532 postmenopausal women aged 65 to 79 years was randomized to daily CE (0.625 mg) plus MPA (2.5 mg) or placebo.

After an average follow-up of 4 years, 40 women in the CE plus MPA group and 21 women in the placebo group were diagnosed with probable dementia. The relative risk of probable dementia for CE plus MPA versus placebo was 2.05 (95 percent CI, 1.21–3.48). The absolute risk of probable dementia for CE plus MPA versus placebo was 45 versus 22 cases per 10,000 women-years. It is unknown whether these findings apply to younger postmenopausal women. (See CLINICAL STUDIES and PRECAUTIONS, Geriatric Use.)

4. Visual Abnormalities

Discontinue estrogen plus progestin therapy pending examination if there is sudden partial or complete loss of vision, or a sudden onset of proptosis, diplopia or migraine. If examination reveals papilledema or retinal vascular lesions, estrogen plus progestin therapy should be permanently discontinued.

PRECAUTIONS

A. General

1. Addition of a progestin when a woman has not had a hysterectomy

Studies of the addition of a progestin for 10 or more days of a cycle of estrogen administration, or daily with estrogen in a continuous regimen, have reported a lowered incidence of endometrial hyperplasia than would be induced by estrogen treatment alone. Endometrial hyperplasia may be a precursor to endometrial cancer.

There are, however, possible risks that may be associated with the use of progestins with estrogens compared to estrogen-alone regimens. These include an increased risk of breast cancer.

2. Unexpected abnormal vaginal bleeding

In cases of unexpected abnormal vaginal bleeding, adequate diagnostic measures are indicated.

3. Elevated blood pressure

Blood pressure should be monitored at regular intervals with estrogen plus progestin therapy.

4. Hypertriglyceridemia

In women with pre-existing hypertriglyceridemia, estrogen plus progestin therapy may be associated with elevations of plasma triglycerides leading to pancreatitis. Consider discontinuation of treatment if pancreatitis occurs.

5. Hepatic Impairment and/or past history of cholestatic jaundice

Estrogens plus progestins may be poorly metabolized in women with impaired liver function. For women with a history of cholestatic jaundice associated with past estrogen use or with pregnancy, caution should be exercised, and in the case of recurrence, medication should be discontinued.

6. Fluid Retention

Progestins may cause some degree of fluid retention. Women who have conditions which might be influenced by this factor, such as cardiac or renal impairment, warrant careful observation when estrogen plus progestin are prescribed.

7. Hypocalcemia

Estrogen plus progestin therapy should be used with caution in women with hypoparathyroidism as estrogen-induced hypocalcemia may occur.

8. Exacerbation of other conditions

Estrogen plus progestin therapy may cause an exacerbation of asthma, diabetes mellitus, epilepsy, migraine, porphyria, systemic lupus erythematosus, and hepatic hemangiomas and should be used with caution in women with these conditions.

B. Patient Information

Physicians are advised to discuss the Patient Information leaflet with women for whom they prescribe PROVERA.

There may be an increased risk of minor birth defects in children whose mothers are exposed to progestins during the first trimester of pregnancy. The possible risk to the male baby is hypospadias, a condition in which the opening of the penis is on the underside rather than the tip of the penis. This condition occurs naturally in approximately 5 to 8 per 1000 male births. The risk may be increased with exposure to PROVERA. Enlargement of the clitoris and fusion of the labia may occur in female babies. However, a clear association between hypospadias, clitoral enlargement and labial fusion with use of PROVERA has not been established.

Inform the patient of the importance of reporting exposure to PROVERA in early pregnancy.

C. Drug-Laboratory Test Interactions

The following laboratory results may be altered by the use of estrogen plus progestin therapy:

1. Accelerated prothrombin time, partial thromboplastin time, and platelet aggregation time; increased platelet count; increased factors II, VII antigen, VIII antigen, VIII coagulant activity, IX, X, XII, VII-X complex, II-VII-X complex, and beta-thromboglobulin; decreased levels of anti-factor Xa and antithrombin III, decreased antithrombin III activity; increased levels of fibrinogen and fibrinogen activity; increased plasminogen antigen and activity.
2. Increased thyroid-binding globulin (TBG) levels leading to increased circulating total thyroid hormone levels as measured by protein-bound iodine (PBI), T4 levels (by column or by radioimmunoassay) or T3 levels by radioimmunoassay, T3 resin uptake is decreased, reflecting the elevated TBG. Free T4 and free T3 concentrations are unaltered. Women on thyroid replacement therapy may require higher doses of thyroid hormone.
3. Other binding proteins may be elevated in serum, for example, corticosteroid binding globulin (CBG), sex hormone binding globulin (SHBG) leading to increased circulating corticosteroid and sex steroids, respectively. Free hormone concentrations, such as testosterone and estradiol, may be decreased. Other plasma proteins may be increased (angiotensinogen/renin substrate, alpha-1-antitrypsin, ceruloplasmin).
4. Increased plasma high-density lipoprotein (HDL) and HDL2 cholesterol subfraction concentrations, reduced low-density lipoprotein (LDL) cholesterol concentration, increased triglycerides levels.
5. Impaired glucose tolerance.

D. Carcinogenesis, Mutagenesis, Impairment of Fertility

Carcinogenicity

Long-term intramuscular administration of medroxyprogesterone acetate has been shown to produce mammary tumors in beagle dogs. There was no evidence of a carcinogenic effect associated with the oral administration of medroxyprogesterone acetate to rats and mice.

Long-term continuous administration of estrogen plus progestin therapy has shown an increased risk of breast cancer and ovarian cancer. (See WARNINGS and PRECAUTIONS.)

Genotoxicity

Medroxyprogesterone acetate was not mutagenic in a battery of in vitro or in vivo genetic toxicity assays.

Fertility

Medroxyprogesterone acetate at high doses is an antifertility drug and high doses would be expected to impair fertility until the cessation of treatment.

E. Pregnancy

PROVERA should not be used during pregnancy. (See CONTRAINDICATIONS.)

There may be increased risks for hypospadias, clitoral enlargement and labial fusion in children whose mothers are exposed to PROVERA during the first trimester of pregnancy. However, a clear association between these conditions with use of PROVERA has not been established.

F. Nursing Mothers

PROVERA should not be used during lactation. Detectable amounts of progestin have been identified in the breast milk of nursing mothers receiving progestins.

G. Pediatric Use

PROVERA tablets are not indicated in children. Clinical studies have not been conducted in the pediatric population.

H. Geriatric Use

There have not been sufficient numbers of geriatric women involved in clinical studies utilizing PROVERA alone to determine whether those over 65 years of age differ from younger subjects in their response to PROVERA alone.

The Women's Health Initiative Studies

In the WHI estrogen plus progestin substudy (daily CE [0.625 mg] plus MPA [2.5 mg] versus placebo), there was a higher relative risk of nonfatal stroke and invasive breast cancer in women greater than 65 years of age. (See CLINICAL STUDIES.)

The Women's Health Initiative Memory Study

In the WHIMS ancillary studies of postmenopausal women 65 to 79 years of age, there was an increased risk of developing probable dementia in women receiving estrogen-alone or estrogen plus progestin when compared to placebo. (See WARNINGS, Probable Dementia.)

Since both ancillary studies were conducted in women 65 to 79 years of age, it is unknown whether these findings apply to younger postmenopausal women. (See WARNINGS, Probable Dementia.)

ADVERSE REACTIONS

See BOXED WARNINGS, WARNINGS, and PRECAUTIONS.

Because clinical trials are conducted under widely varying conditions, adverse reaction rates observed in the clinical trials of a drug cannot be directly compared to rates in the clinical trials of another drug and may not reflect the rates observed in practice.

The following adverse reactions have been reported in women taking PROVERA tablets, without concomitant estrogens treatment:

1. Genitourinary system

Abnormal uterine bleeding (irregular, increase, decrease), change in menstrual flow, breakthrough bleeding, spotting, amenorrhea, changes in cervical erosion and cervical secretions.

2. Breasts

Breast tenderness, mastodynia or galactorrhea has been reported.

3. Cardiovascular

Thromboembolic disorders including thrombophlebitis and pulmonary embolism have been reported.

4. Gastrointestinal

Nausea, cholestatic jaundice.

5. Skin

Sensitivity reactions consisting of urticaria, pruritus, edema and generalized rash have occurred. Acne, alopecia and hirsutism have been reported.

6. Eyes

Neuro-ocular lesions, for example, retinal thrombosis, and optic neuritis.

7. Central nervous system

Mental depression, insomnia, somnolence, dizziness, headache, nervousness.

8. Miscellaneous

Hypersensitivity reactions (for example, anaphylaxis and anaphylactoid reactions, angioedema), rash (allergic) with and without pruritus, change in weight (increase or decrease), pyrexia, edema/fluid retention, fatigue, decreased glucose tolerance.

The following adverse reactions have been reported with estrogen plus progestin therapy.

1. Genitourinary system

Abnormal uterine bleeding/spotting, or flow; breakthrough bleeding; spotting; dysmenorrheal/pelvic pain; increase in size of uterine leiomyomata; vaginitis, including vaginal candidiasis; change in amount of cervical secretion; changes in cervical ectropion; ovarian cancer; endometrial hyperplasia; endometrial cancer.

2. Breasts

Tenderness, enlargement, pain, nipple discharge, galactorrhea; fibrocystic breast changes; breast cancer.

3. Cardiovascular

Deep and superficial venous thrombosis; pulmonary embolism; thrombophlebitis; myocardial infarction; stroke; increase in blood pressure.

4. Gastrointestinal

Nausea, vomiting; abdominal cramps, bloating; cholestatic jaundice; increased incidence of gallbladder disease; pancreatitis; enlargement of hepatic hemangiomas.

5. Skin

Chloasma or melasma that may persist when drug is discontinued; erythema multiforme; erythema nodosum; hemorrhagic eruption; loss of scalp hair; hirsutism; pruritus, rash.

6. Eyes

Retinal vascular thrombosis, intolerance to contact lenses.

7. Central nervous system

Headache; migraine; dizziness; mental depression; chorea; nervousness; mood disturbances; irritability; exacerbation of epilepsy, dementia.

8. Miscellaneous

Increase or decrease in weight; reduced carbohydrate tolerance; aggravation of porphyria; edema; arthalgias; leg cramps; changes in libido; urticaria, angioedema, anaphylactoid/anaphylactic reactions; hypocalcemia; exacerbation of asthma; increased triglycerides.

OVERDOSAGE

Overdosage of estrogen plus progestin therapy may cause nausea and vomiting, breast tenderness, dizziness, abdominal pain, drowsiness/fatigue and withdrawal bleeding may occur in women. Treatment of overdose consists of discontinuation of CE plus MPA together with institution of appropriate symptomatic care.

DOSAGE AND ADMINISTRATION

Secondary Amenorrhea

PROVERA tablets may be given in dosages of 5 or 10 mg daily for 5 to 10 days. A dose for inducing an optimum secretory transformation of an endometrium that has been adequately primed with either endogenous or exogenous estrogen is 10 mg of PROVERA daily for 10 days. In cases of secondary amenorrhea, therapy may be started at any time. Progestin withdrawal bleeding usually occurs within three to seven days after discontinuing PROVERA therapy.

Abnormal Uterine Bleeding Due to Hormonal Imbalance in the Absence of Organic Pathology

Beginning on the calculated 16th or 21st day of the menstrual cycle, 5 or 10 mg of PROVERA may be given daily for 5 to 10 days. To produce an optimum secretory transformation of an endometrium that has been adequately primed with either endogenous or exogenous estrogen, 10 mg of PROVERA daily for 10 days beginning on the 16th day of the cycle is suggested. Progestin withdrawal bleeding usually occurs within three to seven days after discontinuing therapy with PROVERA. Patients with a past history of recurrent episodes of abnormal uterine bleeding may benefit from planned menstrual cycling with PROVERA.

Reduction of Endometrial Hyperplasia in Postmenopausal Women Receiving Daily 0.625 mg Conjugated Estrogens

When estrogen is prescribed for a postmenopausal woman with a uterus, a progestin should also be initiated to reduce the risk of endometrial cancer. A woman without a uterus does not need progestin. Use of estrogen, alone or in combination with a progestin, should be with the lowest effective dose and for the shortest duration consistent with treatment goals and risks for the individual woman. Patients should be re-evaluated periodically as clinically appropriate (for example, 3 to 6 month intervals) to determine if treatment is still necessary (see WARNINGS). For women who have a uterus, adequate diagnostic measures, such as endometrial sampling, when indicated, should be undertaken to rule out malignancy in cases of undiagnosed persistent or recurring abnormal vaginal bleeding.

PROVERA tablets may be given in dosages of 5 or 10 mg daily for 12 to 14 consecutive days per month, in postmenopausal women receiving daily 0.625 mg conjugated estrogens, either beginning on the 1st day of the cycle or the 16th day of the cycle.

Patients should be started at the lowest dose.

The lowest effective dose of PROVERA has not been determined.

HOW SUPPLIED

PROVERA Tablets are available in the following strengths and package sizes:

2.5 mg tablets (scored, round, orange, imprinted PROVERA 2.5)

Bottles of 100: NDC 0009-0065-01

5 mg tablets (scored, round, blue, imprinted PROVERA 5)

Bottles of 100: NDC 0009-0287-01

10 mg tablets (scored, round, white, imprinted PROVERA 10)

Bottles of 100: NDC 0009-0051-01

STORAGE AND HANDLING

Store at controlled room temperature 20° to 25°C (68° to 77°F) [see USP].

"Keep out of reach of children"

Rx only

LAB-0144-10.0
Revised March 2024

PATIENT INFORMATION

PROVERA
(pro-VE-rah)
(medroxyprogesterone acetate tablets, USP)

Read this Patient Information before you start taking PROVERA and read what you get each time you refill your PROVERA prescription. There may be new information. This information does not take the place of talking to your healthcare provider about your medical condition or your treatment.

BOXED WARNING

What is the most important information I should know about PROVERA (a progestin hormone)?

- Do not use estrogens with progestins to prevent heart disease, heart attacks, strokes, or dementia (decline in brain function).
- Using estrogens with progestins may increase your chance of getting heart attacks, strokes, breast cancer, and blood clots.
- Using estrogens with progestins may increase your chance of getting dementia, based on a study of women age 65 years or older.
- You and your healthcare provider should talk regularly about whether you still need treatment with PROVERA.

What is PROVERA?

PROVERA is a medicine that contains medroxyprogesterone acetate, a progestin hormone.

What is PROVERA used for?

PROVERA is used to:

- Treat menstrual periods that have stopped or to treat abnormal uterine bleeding. Women with a uterus who are not pregnant, who stop having regular menstrual periods or who begin to have irregular menstrual periods may have a drop in their progesterone level. Talk with your healthcare provider about whether PROVERA is right for you.
- Reduce your chances of getting cancer of the uterus (womb). In postmenopausal women with a uterus who use estrogens, taking progestin in combination with estrogen will reduce your chance of getting cancer of the uterus (womb).

Who should not take PROVERA?

Do not start taking PROVERA if you:

- have unusual vaginal bleeding
- currently have or have had certain cancers
  Estrogen plus progestin may increase your chance of getting certain types of cancers, including cancer of the breast. If you have or have had cancer, talk with your healthcare provider about whether you should use PROVERA.
- had a stroke or heart attack
- currently have or have had blood clots
- currently have or have had liver problems
- are allergic to PROVERA or any of its ingredients
  See the list of ingredients in PROVERA at the end of this leaflet.
- think you may be pregnant
  PROVERA is not for pregnant women. If you think you may be pregnant, you should have a pregnancy test and know the results. Do not use PROVERA if the test is positive and talk to your healthcare provider. There may be an increased risk of minor birth defects in children whose mothers take PROVERA during the first 4 months of pregnancy.
  PROVERA should not be used as a test for pregnancy.

What should I tell my healthcare provider before taking PROVERA? Before you take PROVERA, tell your healthcare provider if you:

- have any other medical problems
  Your healthcare provider may need to check you more carefully if you have certain conditions such as asthma (wheezing), epilepsy (seizures), diabetes, migraine, endometriosis (severe pelvic pain), lupus, or problems with your heart, liver, thyroid, kidneys, or have high calcium in your blood.
- are going to have surgery or will be on bed rest
  Your healthcare provider will let you know if you need to stop taking PROVERA.
- are breast feeding
  The hormone in PROVERA can pass into your breast milk.

Tell your healthcare provider about all the medicines you take including prescription and nonprescription medicines, vitamins, and herbal supplements. Some medicines may affect how PROVERA works. PROVERA may also affect how other medicines work.

How should I take PROVERA?

Start at the lowest dose and talk to your healthcare provider about how well that dose is working for you. The lowest effective dose of PROVERA has not been determined. You and your healthcare provider should talk regularly (every 3 to 6 months) about the dose you are taking and whether you still need treatment with PROVERA.

1. Absence of menstrual period: PROVERA may be given in doses ranging from 5 to 10 mg daily for 5 to 10 days.
2. Abnormal Uterine Bleeding: PROVERA may be given in doses ranging from 5 to 10 mg daily for 5 to 10 days.
3. Overgrowth of the lining of the uterus: When used in combination with oral conjugated estrogens in postmenopausal women with a uterus, PROVERA may be given in doses ranging from 5 or 10 mg daily for 12 to 14 straight days per month.

What are the possible side effects of PROVERA?

The following side effects have been reported with the use of PROVERA alone:

- breast tenderness
- breast milk secretion
- breakthrough bleeding
- spotting (minor vaginal bleeding)
- irregular periods
- amenorrhea (absence of menstrual periods)
- vaginal secretions
- headaches
- nervousness
- dizziness
- depression
- insomnia, sleepiness, fatigue
- premenstrual syndrome-like symptoms
- thrombophlebitis (inflamed veins)
- blood clot
- itching, hives, skin rash
- acne
- hair loss, hair growth
- abdominal discomfort
- nausea
- bloating
- fever
- increase in weight
- swelling
- changes in vision and sensitivity to contact lenses

Call your healthcare provider right away if you get hives, problems breathing, swelling of the face, mouth, tongue or neck

The following side effects have been reported with the use of PROVERA with an estrogen.

Side effects are grouped by how serious they are and how often they happen when you are treated.

Serious, but less common side effects include:

- heart attack
- stroke
- blood clots
- dementia
- breast cancer
- cancer of the uterus
- cancer of the ovary
- high blood pressure
- high blood sugar
- gallbladder disease
- liver problems
- changes in your thyroid hormone levels
- enlargements of benign tumors ("fibroids")

Call your healthcare provider right away if you get any of the following warning signs or any other unusual symptoms that concern you:

- new breast lumps
- unusual vaginal bleeding
- changes in vision and speech
- sudden new severe headaches
- severe pains in your chest or legs with or without shortness of breath, weakness and fatigue
- memory loss or confusion

Less serious, but common side effects include:

- headache
- breast pain
- irregular vaginal bleeding or spotting
- stomach or abdominal cramps, bloating
- nausea and vomiting
- hair loss
- fluid retention
- vaginal yeast infection

These are not all the possible side effects of PROVERA with or without estrogen. For more information, ask your healthcare provider or pharmacist for advice about side effects. Tell your healthcare provider if you have side effect that bothers you or does not go away. You may report side effects to Pfizer at 1-800-438-1985 or FDA at 1-800-FDA-1088.

What can I do to lower my chances of a serious side effect with PROVERA?

- Talk with your healthcare provider regularly about whether you should continue taking PROVERA. The addition of a progestin is generally recommended for women with a uterus to reduce the chance of getting cancer of the uterus (womb).
- See your healthcare provider right away if you get vaginal bleeding while taking PROVERA.
- Have a pelvic exam, breast exam and mammogram (breast X-ray) every year unless your healthcare provider tells you something else. If members of your family have had breast cancer or if you have ever had breast lumps or an abnormal mammogram, you may need to have breast exams more often.
- If you have high blood pressure, high cholesterol (fat in the blood), diabetes, are overweight, or if you use tobacco, you may have a higher chance of getting heart disease. Ask your healthcare provider for ways to lower your chance of getting heart disease.

General information about safe and effective use of PROVERA

- Medicines are sometimes prescribed for conditions that are not mentioned in patient information leaflets.
- Do not take PROVERA for conditions for which it was not prescribed.
- Do not give PROVERA to other people, even if they have the same symptoms you have. It may harm them.

Keep PROVERA out of the reach of children.

This leaflet provides a summary of the most important information about PROVERA. If you would like more information, talk with your health care provider or pharmacist. You can ask for information about PROVERA that is written for health professionals. You can get more information by calling the toll-free number, 1-800-438-1985.

What are the ingredients in PROVERA?

Each PROVERA tablet for oral administration contains 2.5 mg, 5 mg or 10 mg of medroxyprogesterone acetate and the following inactive ingredients:

Calcium stearate, corn starch, lactose, mineral oil, sucrose and talc.

The 2.5 mg tablets also contain: FD&C Yellow No. 6.

The 5 mg tablets also contain: FD&C Blue No.2 – Aluminum Lake.

This product's labeling may have been updated. For the most recent prescribing information, please visit www.pfizer.com.

Rx only

LAB-0365-9.0
Revised March 2024

PRINCIPAL DISPLAY PANEL - 2.5 mg Tablet Bottle Label - NDC 0065

Pfizer
NDC 0009-0065-01

Provera®
medroxyprogesterone
acetate tablets, USP

2.5 mg

100 Tablets
Rx only

Distributed by: Pharmacia & Upjohn Co
Division of Pfizer Inc, NY, NY 10017

PRINCIPAL DISPLAY PANEL - 5 mg Tablet Bottle Label - 0287

Pfizer

NDC 0009-0287-01

Provera®
medroxyprogesterone
acetate tablets, USP

5 mg

100 Tablets
Rx only

Distributed by: Pharmacia & Upjohn Co
Division of Pfizer Inc, NY, NY 10017

PRINCIPAL DISPLAY PANEL - 10 mg Tablet Bottle Label - 0051

Pfizer

NDC 0009-0051-01

Provera®
medroxyprogesterone
acetate tablets, USP

10 mg

100 Tablets
Rx only

Distributed by: Pharmacia & Upjohn Co
Division of Pfizer Inc, NY, NY 10017